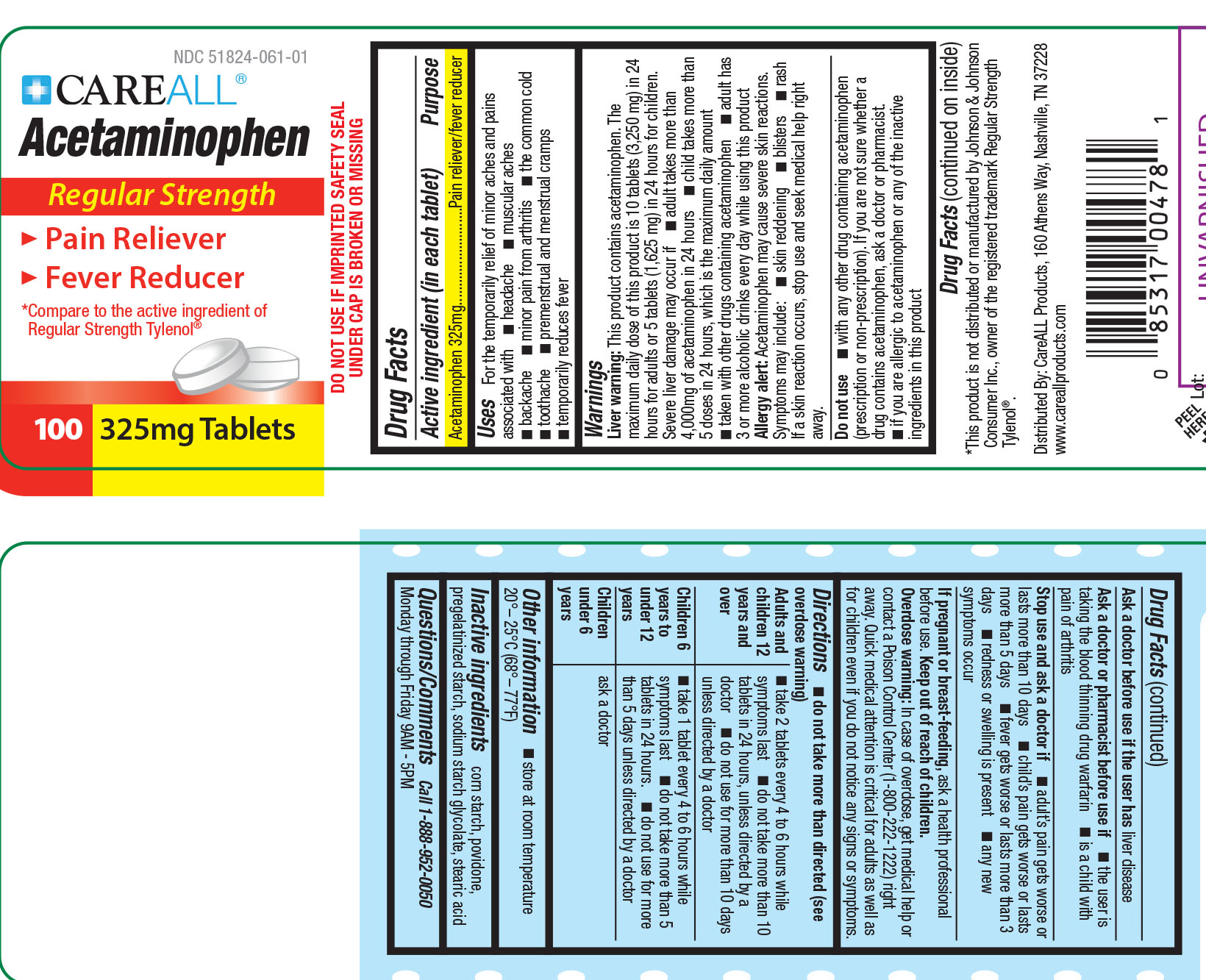 DRUG LABEL: CareALL Acetaminophen
NDC: 51824-061 | Form: TABLET
Manufacturer: New World Imports, Inc
Category: otc | Type: HUMAN OTC DRUG LABEL
Date: 20251222

ACTIVE INGREDIENTS: ACETAMINOPHEN 325 mg/1 1
INACTIVE INGREDIENTS: STARCH, CORN; STEARIC  ACID; POVIDONE; SODIUM STARCH GLYCOLATE TYPE A CORN

Drug Facts

Active Ingredient

Acetaminophen 325mg

Purpose

Pain reliever / Fever reducer

Keep out of reach of children. Overdose warning:In case of overdose, contact a doctor or Poison Control Center immediately. Quick medical attention is critical for adults as well as for children even if you do not notice any signs or symptoms.

Uses

- Temporary relief of minor aches and pains associated with: headache, muscular aches, backache, minor pain from arthritis, the common cold, toothache, premenstrual and menstrual cramps

- Temporarily reduces fever

WARNINGS

Liver warning:This product contains acetaminophen. The manxium daily dose of this product is 10 tablets (3,250 mg) in 24 hours fro adults or 5 tablets (1,625 mg) in 24 hours for children.

Severe liver damage may occur if:

- Adult takes more than 4,000mg of acetaminphen in 24 hours
- Child takes more than 5 doses in 24 hours
- Taken with other drugs containing acetaminophen
- Adult has 3 or more alcoholic drinks every day while using this product

Allergy Alert:Acetaminophen may cause severe skin reactions. Symptoms may include: skin reddening, blisters or rash. If a skin reaction occurs, stop use and seek medical help right away.

Do not use:

- with any other drug containing acetaminophen (prescription or nonprescription).
- If you are allergic to acetaminophen.

Ask a doctor before use if user has:liver disease

Ask a doctor or pharmacist before use if:

- the user is taking the blood thinnig drug warfarin.
- is a child with pain of arthritis

Stop use and ask a doctor if:

- Adults pain gets worse or lasts for more than 10 days.
- Childs pain gets worse or last fr more than 5 days.
- Fever gets worse or lasts for more than 3 days.
- New symptoms occur.
- Redness or swelling is present.

If pregnant or breast-feeding,ask a health professional before use.

Overdose warning:taking more than the recommended dose (overdose) may cause liver damage. In case of overdose, get medical help or contact a Poison Control Center (1-800-222-1222) right away. Quick medical action is critical for adults as well as for children, even if you do not notice any signs or symptoms.

DOSAGE AND ADMINISTRATION

Adults and children 12 years of age and older: Take 2 tablets every 4 to 6 hours while symptoms last. Do not take more than 10 tablets in 24 hours, unless directed by a doctor. do not take for more than 10 days unless directed by a doctor.

Children 6-11 years of age:Take 1 tablet every 4 to 6 hours while symptoms last. Do not take more than 5 tablets in 24 hours. Do not use more than 5 days unless directed by a doctor.

Children under 6 years of age: Ask a doctor

INACTIVE INGREDIENT

Corn starch, povidone, pregelatinized starch, sodium starch glycolate, stearic acid